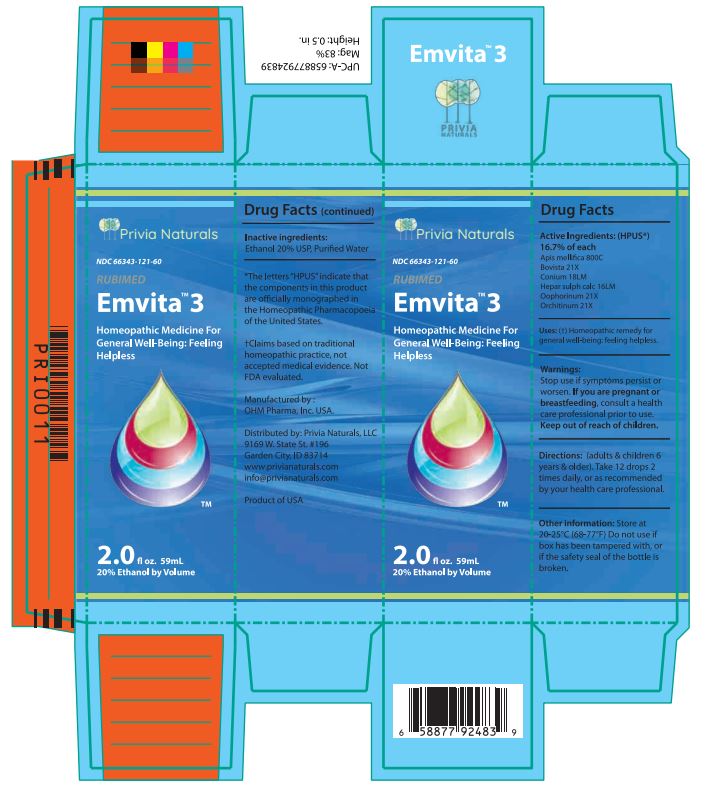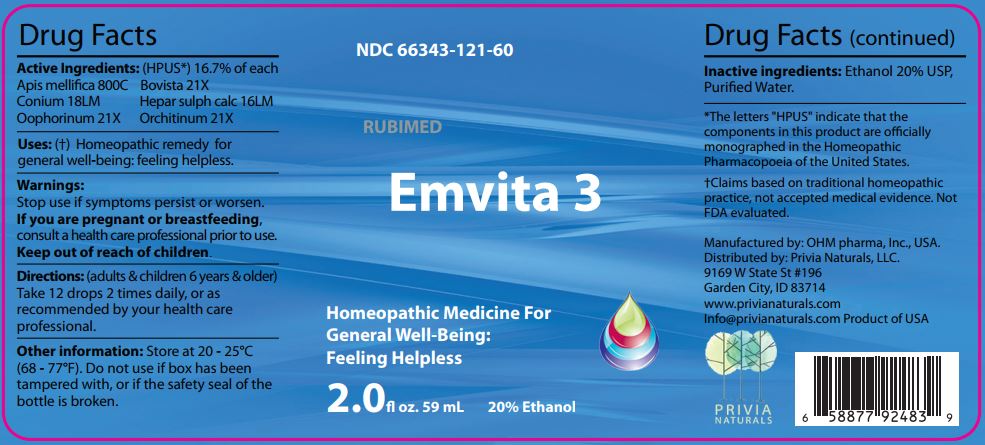 DRUG LABEL: Emvita 3
NDC: 66343-121 | Form: LIQUID
Manufacturer: RUBIMED AG
Category: homeopathic | Type: HUMAN OTC DRUG LABEL
Date: 20241029

ACTIVE INGREDIENTS: APIS MELLIFERA 800 [hp_C]/60 mL; LYCOPERDON UTRIFORME FRUITING BODY 21 [hp_X]/60 mL; CONIUM MACULATUM FLOWERING TOP 18 [hp_M]/60 mL; CALCIUM SULFIDE 16 [hp_M]/60 mL; SUS SCROFA OVARY 21 [hp_X]/60 mL; BOS TAURUS TESTICLE 21 [hp_X]/60 mL
INACTIVE INGREDIENTS: ALCOHOL; WATER

Emvita 3

ACTIVE INGREDIENT

Drug Facts Active Ingredients: (HPUS*) 16.7% of each

Apis mellifica 800C Bovista 21X
Conium 18LM Hepar sulph calc 16LM
Oophorinum 21X Orchitinum 21X

*The letters "HPUS" indicate that the components in this product are officially monographed in the Homeopathic Pharmacopoeia of the United States. †Claims based on traditional homeopathic practice, not accepted medical evidence. Not FDA evaluated.

INDICATIONS AND USAGE

Uses: (†) Homeopathic remedy for feeling helpless.

Warnings:

Stop use if symptoms persist or worsen.

If you are pregnant or breastfeeding,consult a healthcare professional prior to use.

Keep out of reach of children.

DOSAGE AND ADMINISTRATION

Directions: (adults & children 6 years & older)

Take 12 drops 2 times daily, or as recommended by your health care professional.

Other information: Store at 20 - 25°C

(68 - 77°F.) Do not use if box has been

tampered with, or if the safety seal of the

bottle is broken.

Inactive ingredients:Ethanol 20% USP,

Purified Water.

QUESTIONS

Manufactured by: OHM pharma, Inc, USA.

Distributed by: Privia Naturals, LLC.

9169 W State St #196

Garden City, ID 83714

www.privianaturals.com

Info@privianaturals.com Product of USA.

PACKAGE LABEL

NDC 66343-121-60

RUBIMED

Emvita 3

Homeopathic Medicine For

Feeling Helpless

2.0 fl oz. 59mL 20% Ethanol

PURPOSE

Homeopathic Medicine For

Feeling Helpless